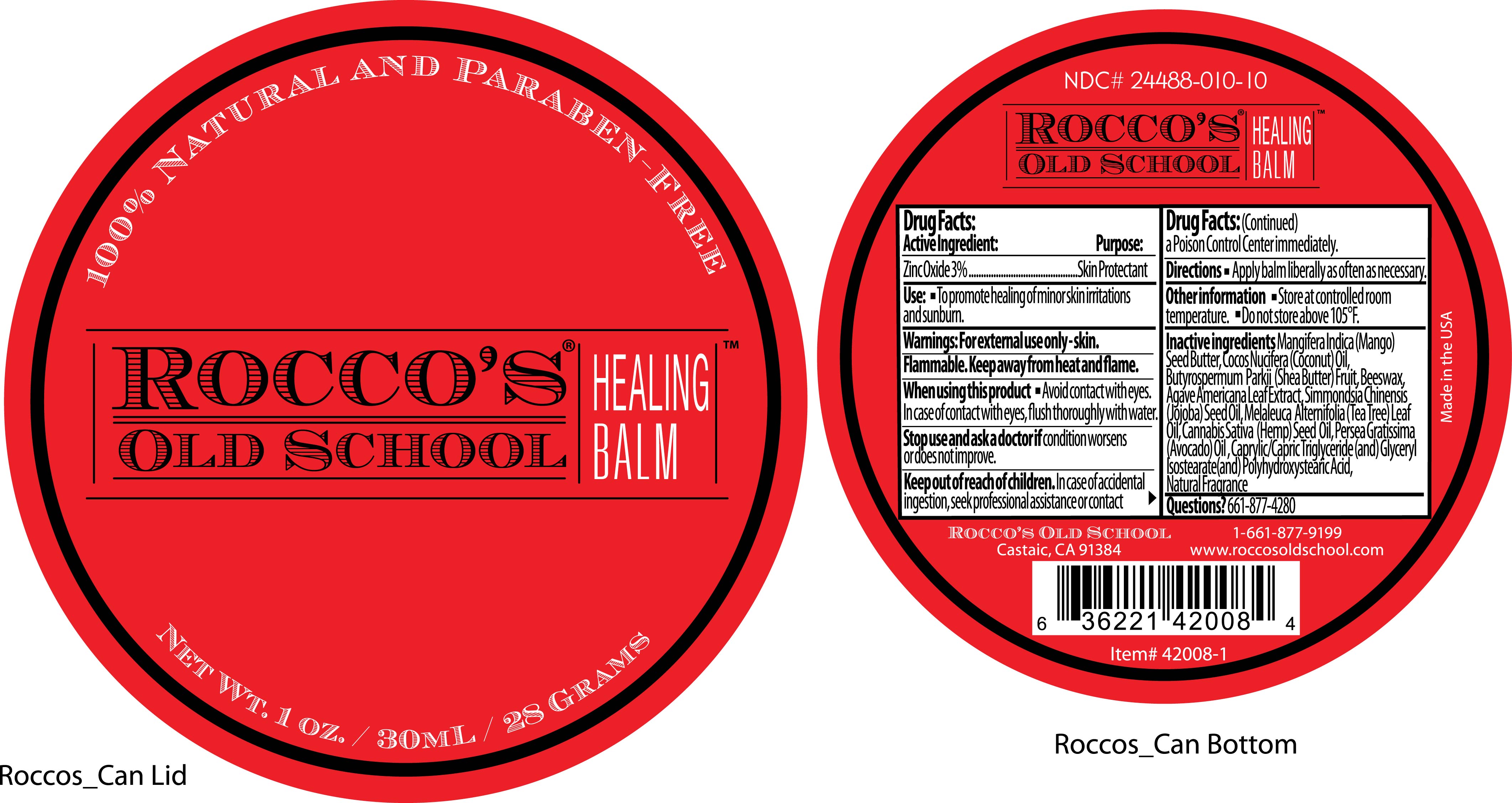 DRUG LABEL: Roccos Old School
NDC: 24488-010 | Form: CREAM
Manufacturer: Roccos Old School
Category: otc | Type: HUMAN OTC DRUG LABEL
Date: 20110217

ACTIVE INGREDIENTS: ZINC OXIDE .9 mL/30 mL
INACTIVE INGREDIENTS: MANGIFERA INDICA SEED BUTTER; COCONUT OIL; SHEANUT; YELLOW WAX; AGAVE AMERICANA LEAF; JOJOBA OIL; TEA TREE OIL; CANNABIS SATIVA SEED OIL; AVOCADO OIL; MEDIUM-CHAIN TRIGLYCERIDES; GLYCERYL ISOSTEARATE; POLYHYDROXYSTEARIC ACID (2300 MW); COCONUT ; LIME; VERBENA HASTATA ROOT

Drug Facts

Active Ingredient: Purpose:

Zince Oxide 3%................................Skin Prorectant

Use:

- To promote healing of minor skin irritations and sunburn.

Warnings:

For external use only-skin. Flammable. Keep away from heat and flame.

When using this product

- Avoid contact with the eyes. In case of contact with eyes, flush thoroughly with water.

Stop use and ask a doctor if

condition worses or does not improve.

Keep out of reach of children.

In case of accidental ingestion, seek professional assistance or contact a Poison Control Center Immediately.

Directions

- Apply balm liberally as often as necessary.

Other information

- Store at controlled room temperature.
- Do not store above 105°F.

Inactive ingredients

Mangifera Indica (Mango) Seed Butter, Cocos Nucifera (Coconut) Oil, Butyrospermum Parkii (Shea Butter) Fruit, Beeswax, Agave Americana Leaf Extract, Simmondsia Chinensis (Jojoba) Seed Oil, Melaleuca Alternifolia (Tea Tree) Leaf Oil, Cannibis Sativia (Hemp) Seed Oil, Persea Gratissima (Avocado) Oil, Caprylic/Capric Triglyceride (and) Gylceryl Isostearate (and) Polyhydroxystearic Acid, and Natural Fragrance

Questions?

661-877-4280

PACKAGE LABEL

Placeholder Text